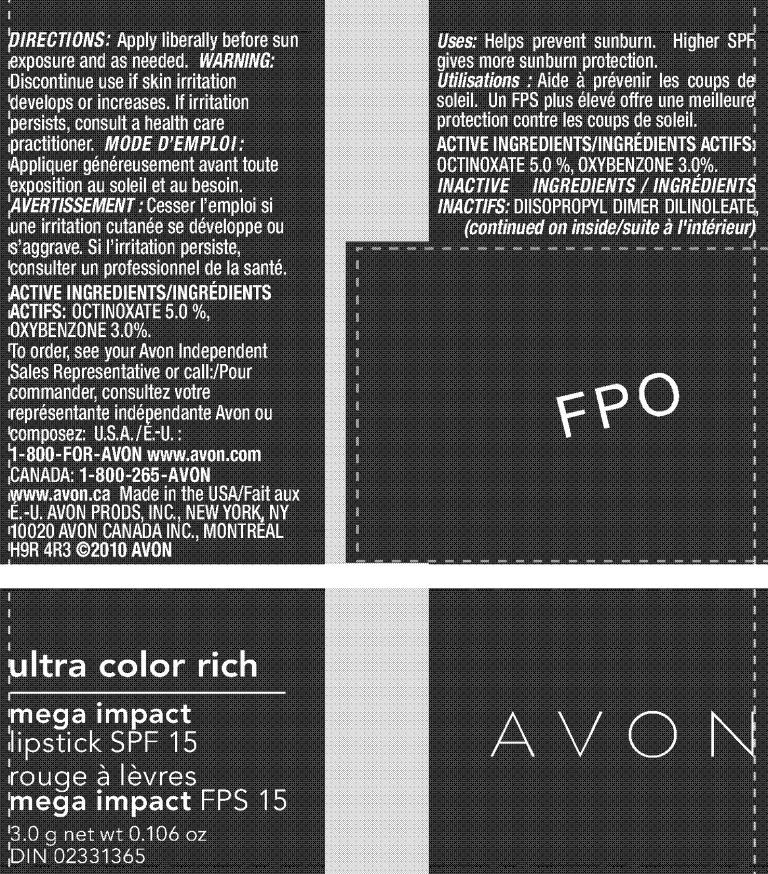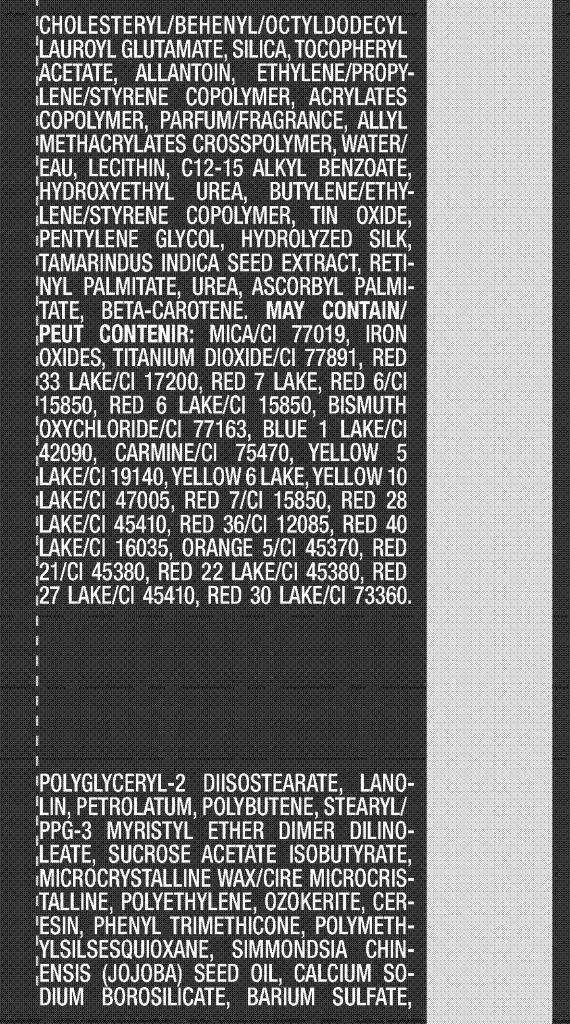 DRUG LABEL: Ultra Color Rich
NDC: 10096-0188 | Form: LIPSTICK
Manufacturer: Avon Products, Inc.
Category: otc | Type: HUMAN OTC DRUG LABEL
Date: 20091222

ACTIVE INGREDIENTS: OCTINOXATE 150 mg/3 g; OXYBENZONE 90 mg/3 g
INACTIVE INGREDIENTS: LANOLIN; PETROLATUM; PHENYL TRIMETHICONE; BARIUM SULFATE; ALLANTOIN; WATER; C12-15 ALKYL BENZOATE; PENTYLENE GLYCOL; UREA; ASCORBYL PALMITATE ; BETA CAROTENE; MICA; TITANIUM DIOXIDE; BISMUTH OXYCHLORIDE

DOSAGE AND ADMINISTRATION

DIRECTIONS: Apply liberally before sun
exposure and as needed.

WARNING:
Discontinue use if skin irritation
develops or increases. If irritation
persists, consult a health care
practitioner.

ACTIVE INGREDIENTS/INGRÉDIENTS
ACTIFS: OCTINOXATE 5.0 %,
OXYBENZONE 3.0%.

INDICATIONS AND USAGE

Uses:Helps prevent sunburn. Higher SPF
gives more sunburn protection.

INACTIVE INGREDIENTS / INGRÉDIENTS
INACTIFS: DIISOPROPYL DIMER DILINOLEATE
POLYGLYCERYL-2 DIISOSTEARATE
LANOLIN
PETROLATUM
POLYBUTENE
STEARYL/PPG-3 MYRISTYL ETHER DIMER DILINOLEATE
SUCROSE ACETATE ISOBUTYRATE
MICROCRYSTALLINE WAX/CIRE MICROCRISTALLINE
POLYETHYLENE
OZOKERITE
CERESIN
PHENYL TRIMETHICONE
POLYMETHYLSILSESQUIOXANE
SIMMONDSIA CHINENSIS (JOJOBA) SEED OIL
CALCIUM SODIUM BOROSILICATE
BARIUM SULFATE
CHOLESTERYL/BEHENYL/OCTYLDODECYL LAUROYL GLUTAMATE
SILICA
TOCOPHERYL ACETATE
ALLANTOIN
ETHYLENE/PROPYLENE/STYRENE COPOLYMER
ACRYLATES COPOLYMER
PARFUM/FRAGRANCE
ALLYL METHACRYLATES CROSSPOLYMER
WATER/EAU
LECITHIN
C12-15 ALKYL BENZOATE
HYDROXYETHYL UREA
BUTYLENE/ETHYLENE/STYRENE COPOLYMER
TIN OXIDE
PENTYLENE GLYCOL
HYDROLYZED SILK
TAMARINDUS INDICA SEED EXTRACT
RETINYL PALMITATE
UREA
ASCORBYL PALMITATE
BETA-CAROTENE
MAY CONTAIN:
MICA/CI 77019
IRON OXIDES
TITANIUM DIOXIDE/CI 77891
RED 33 LAKE/CI 17200
RED 7 LAKE
RED 6/CI 15850
RED 6 LAKE/CI 15850
BISMUTH OXYCHLORIDE/CI 77163
BLUE 1 LAKE/CI 42090
CARMINE/CI 75470
YELLOW 5 LAKE/CI 19140
YELLOW 6 LAKE
YELLOW 10 LAKE/CI 47005
RED 7/CI 15850
RED 28 LAKE/CI 45410
RED 36/CI 12085
RED 40 LAKE/CI 16035
ORANGE 5/CI 45370
RED 21/CI 45380
RED 22 LAKE/CI 45380
RED 27 LAKE/CI 45410
RED 30 LAKE/CI 73360